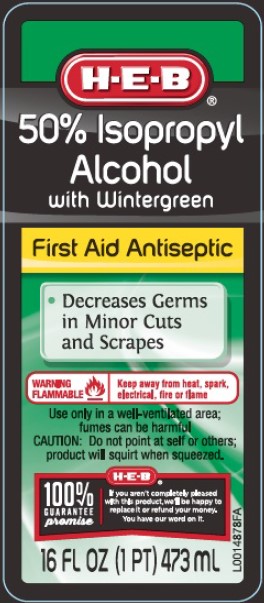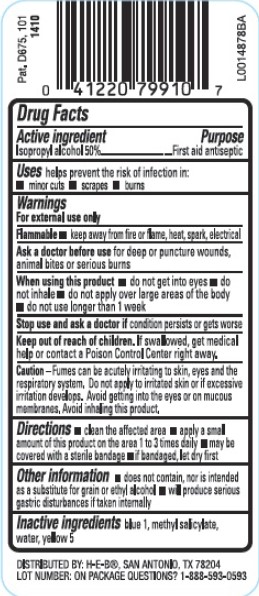 DRUG LABEL: Isopropyl
NDC: 37808-055 | Form: SOLUTION
Manufacturer: H E B
Category: otc | Type: HUMAN OTC DRUG LABEL
Date: 20260224

ACTIVE INGREDIENTS: ISOPROPYL ALCOHOL 50 mL/100 mL
INACTIVE INGREDIENTS: FD&C BLUE NO. 1; METHYL SALICYLATE; WATER; FD&C YELLOW NO. 5

HEB 211.002/211AD
50% Isopropyl Alcohol with Wintergreen

Active ingredient

Isopropyl Alcohol 50%

Purpose

First aid antiseptic

Uses

helps prevent the risk of infection in:

- minor cuts
- scrapes
- burns

Warnings

For external use only

Flammable

- keep away from fire or flame, heat, spark, electrical

Ask a doctor before use

for deep or puncture wounds, animal bites or serious burns

when using this product

- do not get into eyes
- do not inhale
- do not apply over large areas of the body
- do not use longer than 1 week

stop use and ask a doctor if

condition persists or gets worse

Keep out of reach of children.

if swallowed, get medical help or contact a Poison Control Center right away.

Caution

Fumes can be acutely irritating to skin, eyes and the respiratory system. Do not apply to irritated skin or if excessive irritation develops. Avoid getting into the eyes or on mucous membranes. Avoid inhaling this product.

Directions

- clean the affected area
- apply a small amount of this product on the area 1 to 3 times daily
- may be covered with a sterile bandage
- if bandaged, let dry first

Other information

- does not contain, nor is intended as a substitute for grain or ethyl alcohol
- will produce serious gastric distrurbances if taken internally

Inactive ingredients

blue 1, methyl salicylate, water, yellow 5

adverse reaction

DISTRIBUTED BY: H-E-B, SAN ANTONIO, TX 78204

LOT NUMBER: ON PACKAGE QUESTIONS? 1-888-593-0593

principal display panel

H-E-B®

50% ISOPROPYL

Alcohol

with Wintergreen

First Aid Antiseptic

- Decreases Germs in Minor Cuts and Scrapes

WARNING FLAMMABLE - Keep away from heat, spark, electrical, fire or flame

Use only in a well-ventilated area; fumes can be harmful

CAUTION: Do not point at self or others; product will squirt when squeezed

100% GUARANTEE promise

If you aren't completely pleased with the product, we'll be happy to replace it or refund your money. You have our word on it.

16 FL OZ (1 PT) 473 mL